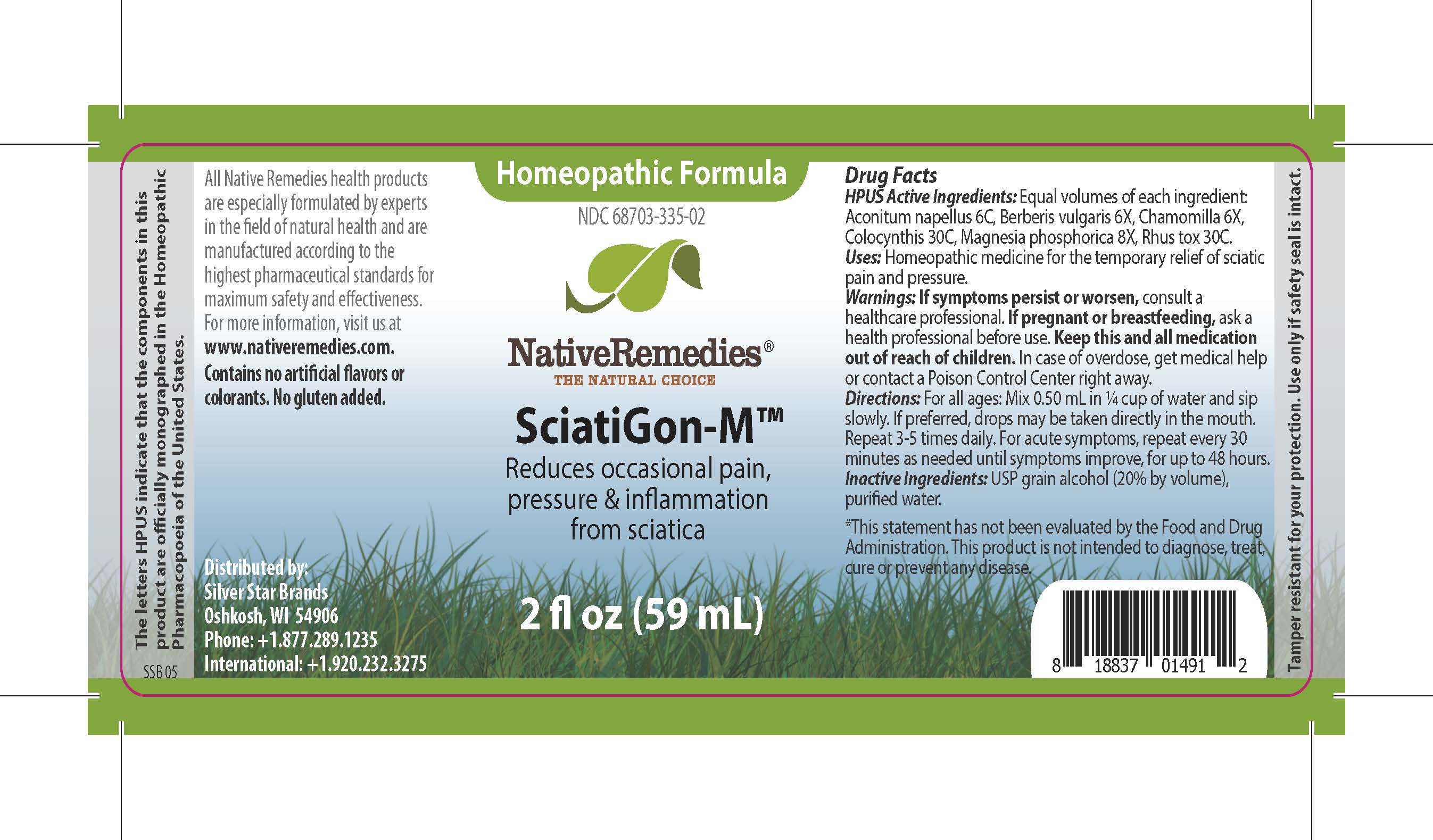 DRUG LABEL: SciatiGon-M
NDC: 68703-335 | Form: LIQUID
Manufacturer: Silver Star Brands
Category: homeopathic | Type: HUMAN OTC DRUG LABEL
Date: 20241203

ACTIVE INGREDIENTS: TOXICODENDRON RADICANS LEAF 30 [hp_C]/59 mL; MAGNESIUM PHOSPHATE, DIBASIC TRIHYDRATE 8 [hp_X]/59 mL; ACONITUM NAPELLUS 6 [hp_C]/59 mL; CITRULLUS COLOCYNTHIS FRUIT 30 [hp_C]/59 mL; BERBERIS VULGARIS FRUIT 6 [hp_X]/59 mL; MATRICARIA RECUTITA 6 [hp_X]/59 mL
INACTIVE INGREDIENTS: ALCOHOL; WATER

NativeRemedies® Sciatigon-M™

HPUS Active Ingredients: Equal volumes of each ingredient: Aconitum napellus 6C, Berberis vulgaris 6X, Chamomilla 6X, Colocynthis 30C, Magnesia phosphorica 8X, Rhus tox 30C.

The letters HPUS indicate that the components in this product are officially monographed in the Homeopathic Pharmacopoeia of the United States.

Uses

Uses: Homeopathic medicine for the temporary relief of sciatic pain and pressure.

This statement has not been evaluated by the Food and Drug Administration. This product is not intended to diagnose, treat, cure or prevent any disease.

Warnings

Warnings: If symptoms persist or worsen, consult a healthcare professional. If pregnant or breastfeeding, ask a health professional before use. Keep this and all medication out of reach of children. In case of overdose, get medical help or contact a Poison Control Center right away.

Directions

For all ages: Mix 0.50 mL in 1/4 cup of water and sip slowly. If preferred, drops may be taken directly in the mouth. Repeat 3-5 times daily. For acute symptoms, repeat every 30 minutes as needed until symptos improve, for up to 48 hours.

OTHER SAFETY INFORMATION

Contains no artificial flavors or colorants. No gluten added.

Tamper resistant for your protection. Use only if safety seal is intact.

Inactive ingredients

Inactive Ingredients: USP grain alchol (20% by volume), purified water.

KEEP OUT OF REACH OF CHILDREN

Keep this and all medication out of reach of children.

PREGNANCY OR BREAST FEEDING

If pregnant or breastfeeding, ask a health professional before use.

PURPOSE

Redues occasional pain, pressure & inflammation from sciatica.